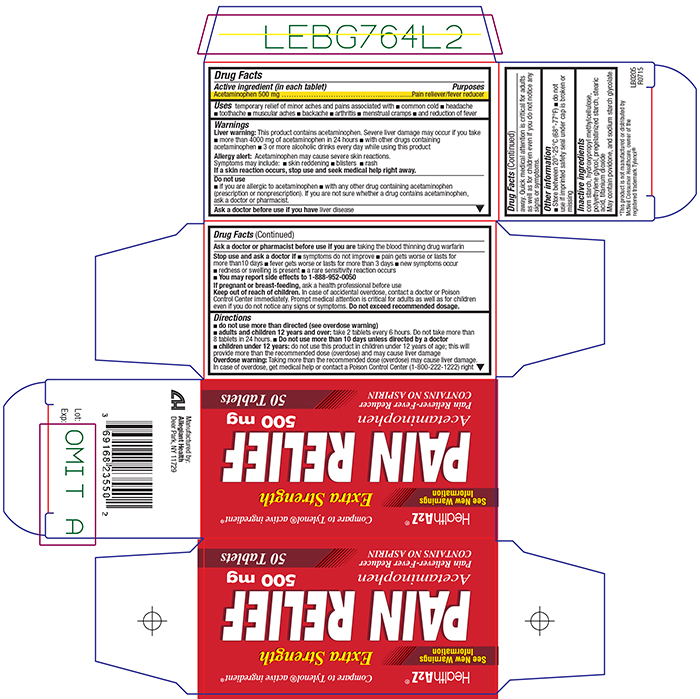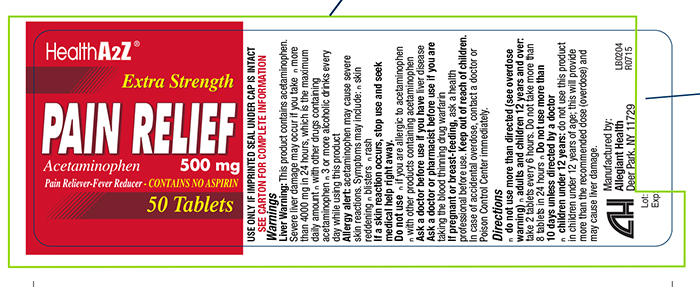 DRUG LABEL: Pain ReliefExtra Strength
NDC: 69168-235 | Form: TABLET
Manufacturer: Allegiant Health
Category: otc | Type: HUMAN OTC DRUG LABEL
Date: 20151228

ACTIVE INGREDIENTS: ACETAMINOPHEN 500 mg/1 1
INACTIVE INGREDIENTS: STARCH, CORN; HYPROMELLOSES; POLYETHYLENE GLYCOLS; STEARIC ACID; TITANIUM DIOXIDE

Drug Facts

Active ingredient

Acetaminophen 500 mg

Purpose

Pain reliever/fever reducer

Uses

temporary relief of minor aches and pains associated with ■ common cold ■ headache ■ toothache ■ muscular aches ■ backache ■ arthritis ■ menstrual cramps ■ and reduction of fever

Warnings

Liver warning: This product contains acetaminophen. Severe liver damage may occur if you takemore than 4000 mg of acetaminophen in 24 hours with other drugs containing acetaminophen 3 or more alcoholic drinks every day while using this product.

Allergy alert: Acetaminophen may cause severe skin reactions.
Symptoms may include: ■ skin reddening ■ blisters ■ rash
If a skin reaction occurs, stop use and seek medical help right away.

Do not use

■ if you are allergic to acetaminophen ■ with any other drug containing acetaminophen (prescription or nonprescription). If you are not sure whether a drug contains acetaminophen, ask a doctor or pharmacist.

Ask a doctor before use if you have

liver disease

Ask a doctor or pharmacist before use if you

are taking the blood thinning drug warfarin

Stop use and ask a doctor if

symptoms do not improve pain gets worse or lasts for more than 10 days ■ fever gets worse or lasts for more than 3 days new symptoms occur redness or swelling is present ■ a rare
sensitivity reaction occurs You may report side effects to 1-888-952-0050

If pregnant or breast-feeding

ask a health professional before use

Ask a doctor before use if you have

liver disease.

Ask a doctor or pharmacist before use if you are

taking the blood thinning drug warfarin.

Stop use and ask a doctor if

■ symptoms do not improve ■ pain gets worse or lasts for more than 10 days ■ fever gets worse or lasts for more than 3 days ■ new symptoms occur ■ redness or swelling is present ■ a rare sensitivity reaction occurs

If you are pregnant or breast-feeding,

ask a health professional before use.

Keep Out of Reach of Children.

In case of accidental overdose, contact a doctor or Poison Control Center immediately. Prompt medical attention is critical for adults as well as for children even if you do not notice any signs or symptoms.
Do not exceed recommended dosage.

Directions

■ do not use more than directed (see overdose warning)
■ adults and children 12 years and over: take 2 tablets every 6 hours. Do not take more than 8 tablets in 24 hours.
■ do not use more than 10 days unless directed by a doctor
■ children under 12 years: do not use this product in children under 12 years of age; this will provide more than the recommended dose (overdose) and may cause liver damage

Overdose warning: Taking more than the recommended dose (overdose) may cause liver damage. In case of overdose, get medical help or contact a Poison Control Center (1-800-222-1222) right away.

Inactive Ingredients

corn starch, hydroxypropyl methylcellulose, polyethylene glycol, pregelatinized starch, stearic acid, titanium dioxide.
May contain povidone, and sodium starch glycolate.

Package/Label Principal Display Panel

Health A2Z® Compare to Tylenol® active ingredient*

See New Warnings Information

Extra Strength
PAIN RELIEF
500mg
Acetaminophen

Pain Reliever-Fever Reducer
CONTAINS NO ASPIRIN

50 Tablets

Health A2Z 235

Label 235